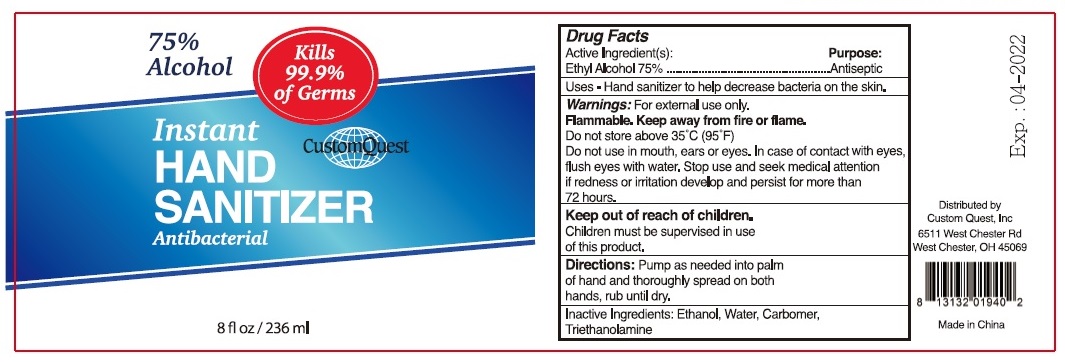 DRUG LABEL: Custom Quest Hand Sanitizer
NDC: 74876-652 | Form: LIQUID
Manufacturer: Custom Quest, Inc.
Category: otc | Type: HUMAN OTC DRUG LABEL
Date: 20200408

ACTIVE INGREDIENTS: ALCOHOL 75 mL/100 mL
INACTIVE INGREDIENTS: WATER; CARBOMER HOMOPOLYMER, UNSPECIFIED TYPE; TROLAMINE

Custom Quest Instant Hand Sanitizer

Active Ingredient(s):

Ethyl Alcohol 75%

Purpose:

Antiseptic

INDICATIONS AND USAGE

Uses - Hand sanitizer to help decrease bacteria on the skin

Warnings: For external use only.

Flammable. Keep away from fire or flame.

Do not store above 35°C (95°F)

Do not use in mouth, ears or eyes. In case of contact, flush eyes with water. Stop use and seek medical attention if redness or irritation develop and persist for more than 72 hours.

Keep out of reach of children.

Children must be supervised in use of this product.

DOSAGE AND ADMINISTRATION

Directions: Pump as needed into palm of hand and thoroughly spread on both hands, rub until dry.

Inactive Ingredients: Ethanol, Water, Carbomer, Triethanolamine

Kills 99.9% of Germs

Antibacterial

Distributed by

Custom Quest, Inc

6511 West Chester Rd

West Chester, OH 45069

Made in China